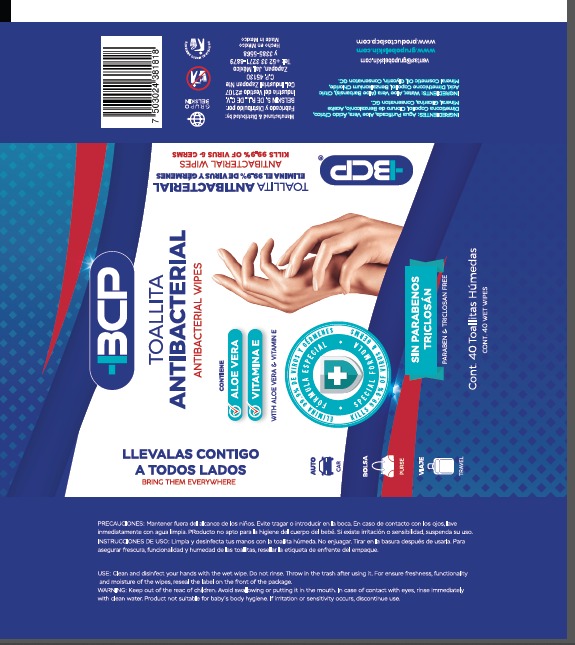 DRUG LABEL: BCP
NDC: 78502-5000 | Form: CLOTH
Manufacturer: BELSKIN S. DE, R.L. DE C.V
Category: otc | Type: HUMAN OTC DRUG LABEL
Date: 20200527

ACTIVE INGREDIENTS: BENZALKONIUM CHLORIDE 0.0025 g/1 g
INACTIVE INGREDIENTS: ALOE VERA LEAF POLYSACCHARIDES 0.05 g/1 g; GLYCERIN 0.05 g/1 g; DIMETHICONE 0.005 g/1 g; CITRIC ACID ACETATE 0.015 g/1 g; MINERAL OIL 0.01 g/1 g; WATER 0.8675 g/1 g

ANTISEPTIC WIPES

CLEANING, DISINFECTIN AND STERILIZATION INSTRUCTIONS

Clean and disinfect your hands with the wet wipe.

Do not rinse.

ENVIRONMENTAL WARNING

Throw in the trash after using it.

KEEP OUT OF REACH OF CHILDREN

WARNING: Keep out of the reach of children.

WARNINGS AND PRECAUTIONS

Avoid swallowing or putting it in the mouth.

In case of contact with eyes, rinse immediately with clean water.

Product not suitable for baby body hygiene.

DOSAGE AND ADMINISTRATION

Clean and disinfect your hands with the wet wipe

INACTIVE INGREDIENTS

INACTIVE INGREDIENTS: WATER, ALOE VERA (ALOE BARBANSIS), CITRIC ACID, DIMETHICONE COPOLYOL, MINERAL COSMETIC OIL, GLYCERIN, CONSERVATON GC.

ACTIVE INGREDIENT

BENZALKONIUM CHLORIDE

INDICATIONS AND USAGE

Clean and disinfect your hands with the wet wipe

PURPOSE

Clean and disinfect your hands with the wet wipe

WARNINGS

WARNING: Keep out of the reach of children.

Avoid swallowing or putting it in the mouth.